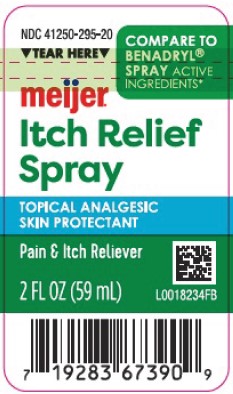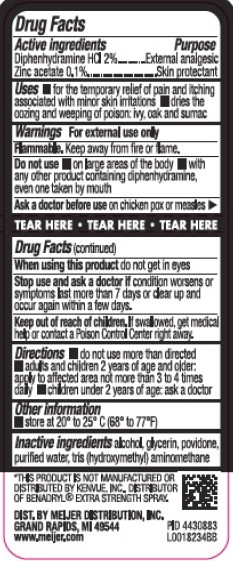 DRUG LABEL: Itch Relief
NDC: 41250-295 | Form: SPRAY
Manufacturer: Meijer, Inc.
Category: otc | Type: HUMAN OTC DRUG LABEL
Date: 20260219

ACTIVE INGREDIENTS: DIPHENHYDRAMINE HYDROCHLORIDE 20 mg/1 mL; ZINC ACETATE 1 mg/1 mL
INACTIVE INGREDIENTS: ALCOHOL; GLYCERIN; POVIDONE; WATER; TROMETHAMINE

Meijer 295.000/295AA-AB
Itch Relief Spray

Active ingredients

Diphenhydramine HCL 2%

Zinc acetate 0.1%

Purpose

External analgesic

Skin protectant

Uses

- for the temporary relief of pain and itching associated with minor skin irritations
- dries the oozing and weeping of poison: ivy, oak, sumac

Warnings

For external use only

Flammable. Keep away from fire or flame.

Do not use

- on large areas of the body
- with any other product containing diphenhydramine, even one taken by mouth

Ask a doctor before use

- on chicken pox or measles

When using this product

do not get in eyes

Stop use and ask a doctor if

condition worsens or symptoms last more than 7 days or clear up and occur again within a few days.

Keep out of reach of children.

If swallowed, get medical help or contact a Poison Control Center right away.

Directions

- do not use more than directed
- adults and children 2 years of age and older: apply to affected area not more than 3 to 4 times daily
- children under 2 years of age: ask a doctor

Other information

store at 20⁰ to 25⁰ C (68⁰ to 77⁰ F)

Inactive ingredients

alcohol, glycerin, povidone, purified water, tris (hydroxymethyl)aminomethane

Disclaimer

*THIS PRODUCT IS NOT MANUFACTURED OR DISTRIBUTED BY KENVUE, INC., DISTRIBUTOR OF BENADRYL®EXTRA STRENGTH SPRAY.

Adverse Reactions

DIST. BY MEIJER DISTRIBUTION, INC.

GRAND RAPIDS, MI 49544

www.meijer.com

principal display panel

NDC 41250-295-20

TEAR HERE

COMPARE TO BENADRYL®SPRAY ACTIVE INGREDIENTS*

meijer®

Itch Relief Spray

TOPICAL ANALGESIC

SKIN PROTECTANT

Pain & Itch Reliever

2 FL OZ (59 mL)